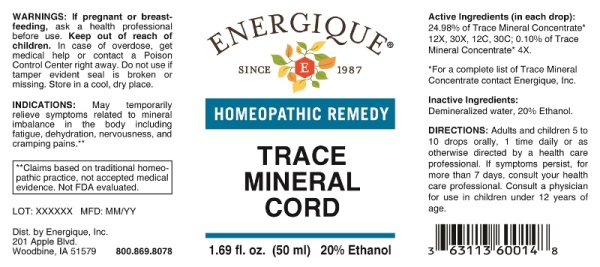 DRUG LABEL: Trace Mineral Cord
NDC: 44911-0263 | Form: LIQUID
Manufacturer: Energique, Inc.
Category: homeopathic | Type: HUMAN OTC DRUG LABEL
Date: 20240927

ACTIVE INGREDIENTS: ACTIVATED CHARCOAL 4 [hp_X]/1 mL; IRON 4 [hp_X]/1 mL; SULFUR 4 [hp_X]/1 mL; MAGNESIUM 4 [hp_X]/1 mL; ALUMINUM 4 [hp_X]/1 mL; CALCIUM 4 [hp_X]/1 mL; SILICON 4 [hp_X]/1 mL; PHOSPHORUS 4 [hp_X]/1 mL; CHLORIDE ION 4 [hp_X]/1 mL; MANGANESE 4 [hp_X]/1 mL; ZINC 4 [hp_X]/1 mL; POTASSIUM 4 [hp_X]/1 mL; LANTHANUM 4 [hp_X]/1 mL; NICKEL 4 [hp_X]/1 mL; SELENIUM 4 [hp_X]/1 mL; BERYLLIUM 4 [hp_X]/1 mL; VANADIUM 4 [hp_X]/1 mL; BORON 4 [hp_X]/1 mL; YTTRIUM 4 [hp_X]/1 mL; STRONTIUM 4 [hp_X]/1 mL; GADOLINIUM 4 [hp_X]/1 mL; COBALT 4 [hp_X]/1 mL; FLUORIDE ION 4 [hp_X]/1 mL; NEODYMIUM 4 [hp_X]/1 mL; CHROMIUM 4 [hp_X]/1 mL; TELLURIUM 4 [hp_X]/1 mL; BROMINE 4 [hp_X]/1 mL; COPPER 4 [hp_X]/1 mL; LITHIUM 4 [hp_X]/1 mL; ANTIMONY 4 [hp_X]/1 mL; TITANIUM 4 [hp_X]/1 mL; ZIRCONIUM 4 [hp_X]/1 mL; RUBIDIUM 4 [hp_X]/1 mL; SODIUM 4 [hp_X]/1 mL; THULIUM 4 [hp_X]/1 mL; MOLYBDENUM 4 [hp_X]/1 mL; SAMARIUM 4 [hp_X]/1 mL; YTTERBIUM 4 [hp_X]/1 mL; IODINE 4 [hp_X]/1 mL; CERIUM 4 [hp_X]/1 mL; DYSPROSIUM 4 [hp_X]/1 mL; PRASEODYMIUM 4 [hp_X]/1 mL; SCANDIUM 4 [hp_X]/1 mL; ERBIUM 4 [hp_X]/1 mL; LUTETIUM 4 [hp_X]/1 mL; GALLIUM 4 [hp_X]/1 mL; THORIUM 4 [hp_X]/1 mL; TUNGSTEN 4 [hp_X]/1 mL; BARIUM 4 [hp_X]/1 mL; TIN 4 [hp_X]/1 mL; BISMUTH 4 [hp_X]/1 mL; HOLMIUM 4 [hp_X]/1 mL; TANTALUM 4 [hp_X]/1 mL; TERBIUM 4 [hp_X]/1 mL; GERMANIUM 4 [hp_X]/1 mL; INDIUM 4 [hp_X]/1 mL; THALLIUM 4 [hp_X]/1 mL; CESIUM 4 [hp_X]/1 mL; RUTHENIUM 4 [hp_X]/1 mL; SILVER 4 [hp_X]/1 mL; EUROPIUM 4 [hp_X]/1 mL; NIOBIUM 4 [hp_X]/1 mL; HAFNIUM 4 [hp_X]/1 mL; RHENIUM 4 [hp_X]/1 mL; GOLD 4 [hp_X]/1 mL; IRIDIUM 4 [hp_X]/1 mL; OSMIUM 4 [hp_X]/1 mL; PALLADIUM 4 [hp_X]/1 mL; PLATINUM 4 [hp_X]/1 mL; RHODIUM 4 [hp_X]/1 mL
INACTIVE INGREDIENTS: WATER; ALCOHOL

Drug Facts:

ACTIVE INGREDIENTS:

(in each drop): 24.98% of Trace Mineral Concentrate* 12X, 30X, 12C; 0.10% of Trace Mineral Concentrate* 4X, Aluminum, Antimony, Barium, Beryllium, Bismuth, Boron, Bromine, Calcium, Carbon, Cerium, Cesium, Chloride, Chromium, Cobalt, Copper, Dysprosium, Erbium, Europium, Fluoride, Gadolinium, Gallium, Germanium, Gold, Hafnium, Holmium, Indium, Iodine, Iridium, Iron, Lanthanum, Lithium, Lutetium, Magnesium, Manganese, Molybdenum, Neodymium, Nickel, Niobium, Osmium, Palladium, Phosphorus, Platinum, Potassium, Praseodymium, Rhenium, Rhodium, Rubidium, Ruthenium, Samarium, Scandium, Selenium, Silicon, Silver, Sodium, Strontium, Sulfur, Tantalum, Tellurium, Terbium, Thallium, Thorium, Thulium, Tin, Titanium, Tungsten, Vanadium, Ytterbium, Yttrium, Zinc, Zirconium 4X, 12X, 30X, 12C, 30C.

INDICATIONS:

May temporarily relieve symptoms related to mineral imbalance in the body including fatigue, dehydration, nervousness, and cramping pains.**

**Claims based on traditional homeopathic practice, not accepted medical evidence. Not FDA evaluated.

WARNINGS:

If pregnant or breast-feeding, ask a health professional before use.

Keep out of reach of children. In case of overdose, get medical help or contact a Poison Control Center right away.

Do not use if tamper evident seal is broken or missing. Store in a cool, dry place.

Keep out of reach of children. In case of overdose, get medical help or contact a Poison Control Center right away.

DIRECTIONS:

Adults and children 5 to 10 drops orally, 1 time daily or as otherwise directed by a health care professional. If symptoms persist for more than 7 days, consult your health care professional. Consult a physician for use in children under 12 years of age.

INDICATIONS:

May temporarily relieve symptoms related to mineral imbalance in the body including fatigue, dehydration, nervousness, and cramping pains.**

**Claims based on traditional homeopathic practice, not accepted medical evidence. Not FDA evaluated.

INACTIVE INGREDIENTS:

Demineralized water, 20% Ethanol.

QUESTIONS:

Dist. by Energique, Inc.,

201 Apple Blvd
Woodbine, IA 51579 800.869.8078

PACKAGE LABEL DISPLAY:

ENERGIQUE

SINCE 1987

HOMEOPATHIC REMEDY

TRACE

MINERAL

CORD

1.69 fl. oz. (50 ml)